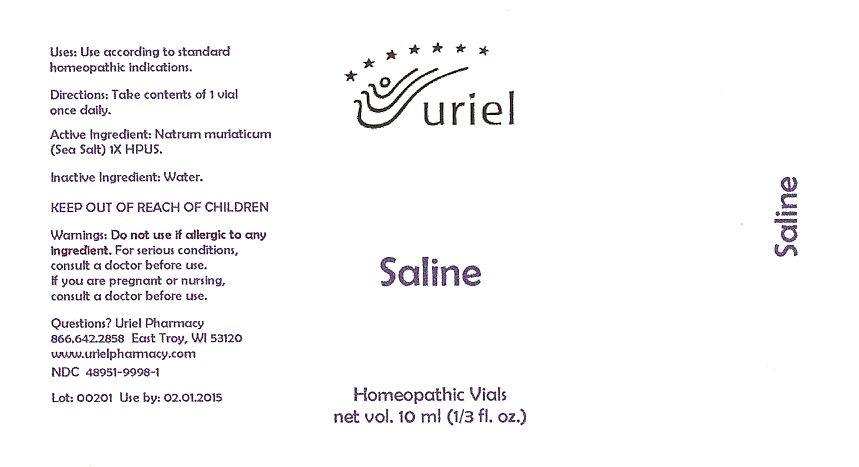 DRUG LABEL: Saline
NDC: 48951-9998 | Form: SOLUTION/ DROPS
Manufacturer: Uriel Pharmacy Inc
Category: homeopathic | Type: HUMAN OTC DRUG LABEL
Date: 20100202

ACTIVE INGREDIENTS: SODIUM CHLORIDE 1 [hp_X]/1 1
INACTIVE INGREDIENTS: WATER

Saline Vials - 10 ml

Purpose

Uses: Use according to standard homeopathic indications.

Dosage & Administration

Directions: Take contents of 1 vial once daily.

OTC-Active Ingredient

Active Ingredient: Natrum muriaticum (Sea Salt) 1X HPUS.

Inactive Ingredient

Inactive Ingredient: Water.

Keep out of reach of children

Do not use section

Warnings:Do not use if allergic to any ingredient.

Ask doctor section

For serious conditions, consult a doctor before use.

Pregnancy or breast feeding section

If you are pregnant or nursing, consult a doctor before use.

Questions section

Questions? Uriel Pharmacy

866 642-2858 East Troy, WI 53120

www.urielpharmacy.com

NDC 48951-9998-1

Principal Display Panel

Saline

Homeopathic Vials

net vol. 10 ml (1/3 fl. oz.)